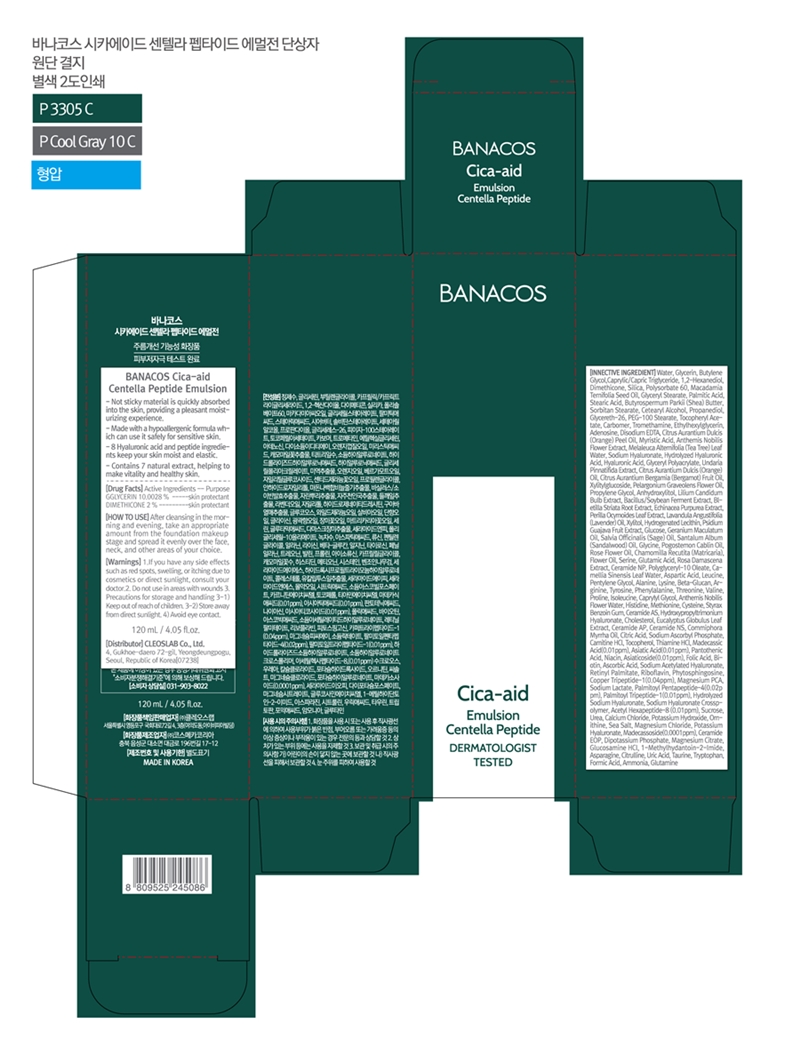 DRUG LABEL: BANACOCica-aid Centella Peptide emulsion
NDC: 79540-314 | Form: LOTION
Manufacturer: Cleoslab Co.,Ltd
Category: otc | Type: HUMAN OTC DRUG LABEL
Date: 20211219

ACTIVE INGREDIENTS: GLYCERIN 10.0028 g/100 mL; DIMETHICONE 2 g/100 mL
INACTIVE INGREDIENTS: MYRISTIC ACID 0.012 mL/100 mL; CHAMAEMELUM NOBILE FLOWER 0.00979999 mL/100 mL; HYALURONATE SODIUM 0.0051 mL/100 mL; HYALURONIC ACID 0.00500025 mL/100 mL; XYLITYLGLUCOSIDE 0.004 mL/100 mL; PERILLA FRUTESCENS LEAF 0.00175 mL/100 mL; GERANIUM MACULATUM ROOT OIL 0.000375 mL/100 mL; ROSA DAMASCENA FLOWER 0.0001 mL/100 mL; CERAMIDE NP 0.0001 mL/100 mL; POLYGLYCERYL-10 OLEATE 0.0001 mL/100 mL; ASPARTIC ACID 0.00007901456 mL/100 mL; CURDLAN 0.00004 mL/100 mL; EUCALYPTUS GLOBULUS LEAF 0.00001 mL/100 mL; TYROSINE 0.00003400692 mL/100 mL; ISOLEUCINE 0.0000270064 mL/100 mL; CHAMAEMELUM NOBILE FLOWER OIL 0.00002 mL/100 mL; CYSTEINE 0.00001150076 mL/100 mL; CERAMIDE 4 0.00001 mL/100 mL; SODIUM ASCORBYL PHOSPHATE 0.000004 mL/100 mL; LEVOCARNITINE HYDROCHLORIDE 0.000001 mL/100 mL; TOCOPHEROL 0.000001 mL/100 mL; THIAMINE HYDROCHLORIDE 0.000001 mL/100 mL; MADECASSIC ACID 0.000001 mL/100 mL; ASIATIC ACID 0.000001 mL/100 mL; PANTOTHENIC ACID 0.000001 mL/100 mL; ASIATICOSIDE 0.000001 mL/100 mL; FOLIC ACID 0.000001 mL/100 mL; BIOTIN 0.000001 mL/100 mL; PHYTOSPHINGOSINE 0.000001 mL/100 mL; MAGNESIUM PIDOLATE 0.0000002628 mL/100 mL; UREA 0.00000007 mL/100 mL; POTASSIUM HYDROXIDE 0.0000000512 mL/100 mL; SEA SALT 0.0000000482 mL/100 mL; MAGNESIUM CHLORIDE 0.0000000234 mL/100 mL; CREATININE 0.000000005 mL/100 mL; MADECASSOSIDE 0.0000000234 mL/100 mL; TRYPTOPHAN 0.000000002 mL/100 mL; CERAMIDE 1 0.00000001 mL/100 mL; CITRULLINE 0.00000000456 mL/100 mL; URIC ACID 0.000000004 mL/100 mL; CAPRYLYL GLYCOL 0.000025 mL/100 mL; PROPYLENE GLYCOL 0.0032 mL/100 mL; ANHYDROXYLITOL 0.0028 mL/100 mL; LILIUM CANDIDUM BULB 0.002 mL/100 mL; HISTIDINE 0.000015018 mL/100 mL; MYRRH OIL 0.00000975 mL/100 mL; CITRIC ACID MONOHYDRATE 0.000005 mL/100 mL; SAGE OIL 0.0003 mL/100 mL; TRICAPRIN 3.0032 mL/100 mL; LAVENDER OIL 0.001575 mL/100 mL; HYDROGENATED SOYBEAN LECITHIN 0.0011 mL/100 mL; GUAVA 0.001 mL/100 mL; ANHYDROUS DEXTROSE 0.0004 mL/100 mL; ROSA RUGOSA FLOWER BUD 0.0001875 mL/100 mL; SERINE 0.0001360992 mL/100 mL; GLUTAMIC ACID 0.00012600548 mL/100 mL; TEA LEAF OIL 0.0001 mL/100 mL; PALMITOYL TRIPEPTIDE-1 0.0000001 mL/100 mL; STYRAX BENZOIN RESIN 0.00001125 mL/100 mL; LEUCINE 0.00006900744 mL/100 mL; SODIUM LACTATE 0.0000002506 mL/100 mL; POTASSIUM PHOSPHATE, DIBASIC 0.00000000916 mL/100 mL; MAGNESIUM CITRATE 0.0000000062 mL/100 mL; GLUCOSAMINE HYDROCHLORIDE 0.000000006 mL/100 mL; ASPARAGINE 0.00000000472 mL/100 mL; SHEA BUTTER 0.500295 mL/100 mL; XYLITOL 0.0012 mL/100 mL; SORBITAN MONOSTEARATE 0.5 mL/100 mL; BUTYLENE GLYCOL 4.01495 mL/100 mL; WATER 70.70259544364 mL/100 mL; PEG-100 STEARATE 0.24 mL/100 mL; CARBOMER HOMOPOLYMER, UNSPECIFIED TYPE 0.16 mL/100 mL; GLYCINE 0.0002450688 g/100 mL; EDETATE DISODIUM ANHYDROUS 0.020002 mL/100 mL; ETHYLHEXYLGLYCERIN 0.05001 mL/100 mL; 1,2-HEXANEDIOL 2.002525 mL/100 mL; SILICON DIOXIDE 1 mL/100 mL; POLYSORBATE 60 1 mL/100 mL; MACADAMIA OIL 1 mL/100 mL; PALMITIC ACID 0.66 mL/100 mL; STEARIC ACID 0.528 mL/100 mL; ADENOSINE 0.04 mL/100 mL; ORANGE OIL 0.015 mL/100 mL; GLYCERYL MONOSTEARATE 0.76 mL/100 mL; PROPANEDIOL 0.485 mL/100 mL; GLYCERETH-26 0.4 mL/100 mL; .ALPHA.-TOCOPHEROL ACETATE 0.2 mL/100 mL; TROMETHAMINE 0.12 mL/100 mL; CERAMIDE NG 0.00001 mL/100 mL; ACETYL HEXAPEPTIDE-8 0.0000001 mL/100 mL; POTASSIUM 0.00000002 mL/100 mL; MEDIUM-CHAIN TRIGLYCERIDES 3.0032 mL/100 mL; CETOSTEARYL ALCOHOL 0.5 mL/100 mL; METHIONINE 0.0000115028 g/100 mL; VITAMIN A PALMITATE 0.000001 mL/100 mL; SODIUM S-(2-HYDROXY-3-(3-(TRIHYDROXYSILYL)PROPOXY)PROPYL) SULFUROTHIOATE 0.0000001 mL/100 mL; CALCIUM CHLORIDE 0.0000000538 mL/100 mL; ORNITHINE 0.00000005 mL/100 mL; TAURINE 0.0000000024 mL/100 mL; AMMONIA 0.000000001 mL/100 mL; ARGININE 0.0000380054 mL/100 mL; TEA TREE OIL 0.0094 mL/100 mL; BERGAMOT OIL 0.0040875 mL/100 mL; BLETILLA STRIATA BULB 0.00175 mL/100 mL; PHENYLALANINE 0.00003200552 mL/100 mL; THREONINE 0.00003002052 mL/100 mL; SODIUM ACETYLATED HYALURONATE 0.000001 mL/100 mL; ALANINE 0.000044042 mL/100 mL; PROLINE 0.00003000996 mL/100 mL; LYSINE 0.00004200828 mL/100 mL; NIACIN 0.000001 mL/100 mL; ASCORBIC ACID 0.000001 mL/100 mL; PREZATIDE COPPER 0.0000004 mL/100 mL; FORMIC ACID 0.0000000012 mL/100 mL; PALMITOYL PENTAPEPTIDE-4 0.0000002 mL/100 mL; GLUTAMINE 0.0000000008 mL/100 mL; CHAMOMILE FLOWER OIL 0.00015 mL/100 mL; RIBOFLAVIN 0.000001 mL/100 mL; ECHINACEA PURPUREA 0.00175 mL/100 mL; UNDARIA PINNATIFIDA 0.005 mL/100 mL; SANDALWOOD OIL 0.0003 mL/100 mL; PELARGONIUM GRAVEOLENS FLOWER OIL 0.003225 mL/100 mL; POGOSTEMON CABLIN LEAF OIL 0.000225 mL/100 mL; PENTYLENE GLYCOL 0.00005 mL/100 mL; VALINE 0.00003001348 mL/100 mL; CHOLESTEROL 0.00001 mL/100 mL; CERAMIDE AP 0.00001 mL/100 mL; SUCROSE 0.0000000838 mL/100 mL

Emulsion

BANACOS Cica-aid Centella Peptide emulsion

METHIONINE
GLYCINE
DIMETHICONE
GLYCERIN

stop use and ask a doctor

Take care not to get into the eye.

If you have any side effects such as red spots, swelling or tiching due to cosmetic or direct sunlight, consult your doctor.

PURPOSE

skinprotect

Warning

For external use only

Keep away from fire of flame

Do not spray on clothes because it can stain.

Be caeful not to get into your eyes, and if so wash thoroughly with water

Keep out of reach of children.

indication

sprinkle evenly on your face

do not us

do not use in areas with wounds.

avoid eye contact

Direction

After cleansing in the morning and evening take an appropriate amount from the foundation makeup stage and spread it evenly over the face, neck, and other areas of your choice.

inactive

PEG-100 STEARATE
CARBOMERmL IACT
EDETATE DISODIUM ANHYDROUS
ETHYLHEXYLGLYCERIN
1,2-HEXANEDIOL
SILICON DIOXIDE
MACADAMIA OIL
PALMITIC ACID
STEARIC ACID

label

79540-314-01